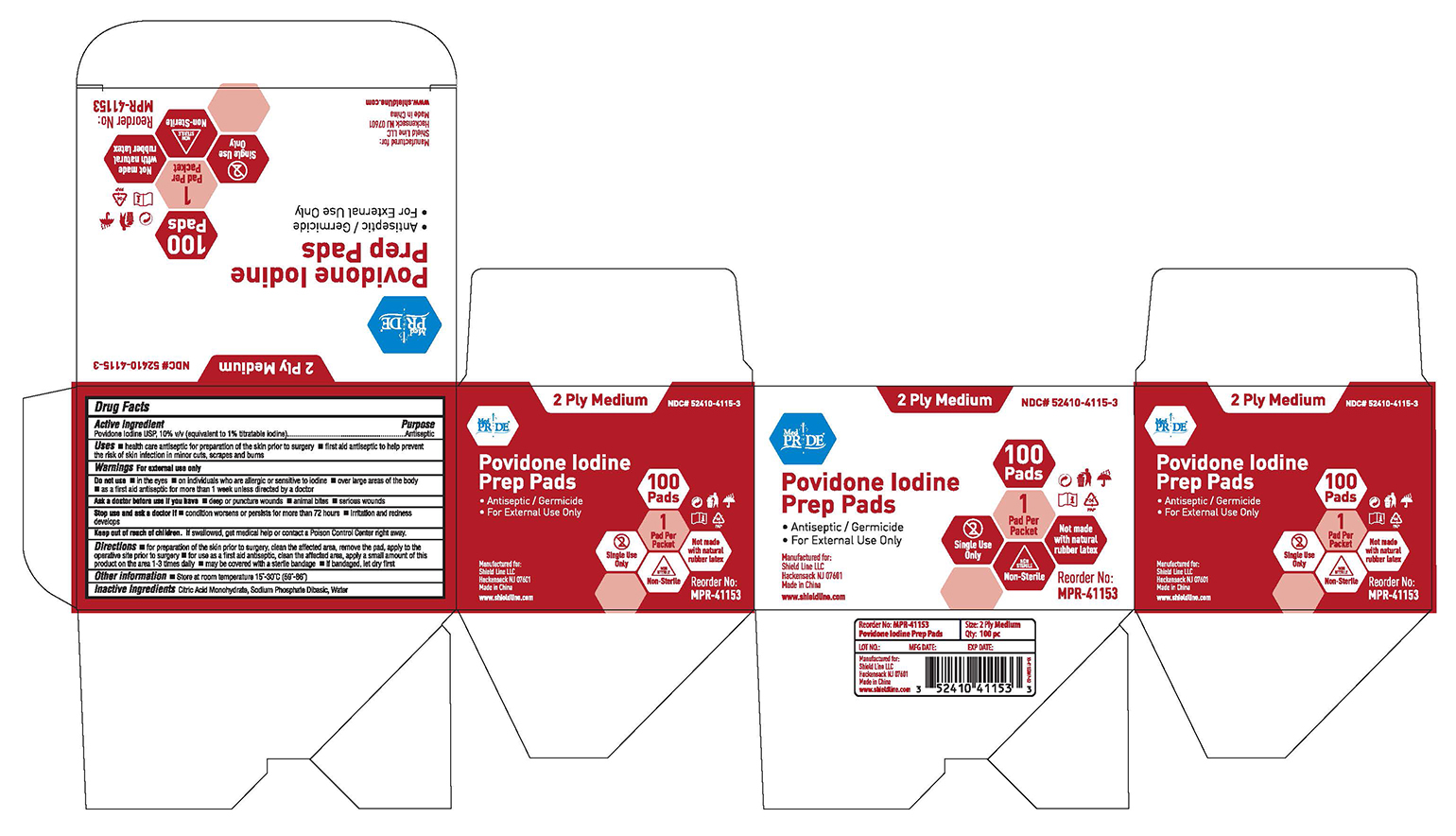 DRUG LABEL: MedPride
NDC: 52410-4115 | Form: SOLUTION
Manufacturer: Shield Line LLC
Category: otc | Type: HUMAN OTC DRUG LABEL
Date: 20250819

ACTIVE INGREDIENTS: POVIDONE-IODINE 0.1 g/1 1
INACTIVE INGREDIENTS: CITRIC ACID MONOHYDRATE; WATER; SODIUM PHOSPHATE, DIBASIC

Drug Facts

Active Ingredient

Povidone Iodine 10% v/v

(equivalent to 1% titratable iodine)

Purpose

Antiseptic

Uses

■ health care antiseptic for preparation of the skin prior to surgery

■ first aid antiseptic to help prevent the risk of skin infection in minor cuts, scrapes and burns

Warnings

For external use only

Do not use

■ in the eyes

■ on individuals who are allergic or sensitive to iodine

■ over large areas of the body

■ as first aid antiseptic for more than 1 week unless directed by doctor

Ask a doctor before use if you have

■ deep or puncture wounds

■ animal bites

■ serious burns

Stop use and ask a doctor if

■ condition worsens or persists fro more than 72 hours ■ irritation and rednesss develops

Keep out of reach of children

If swallowed, get medical help or contact a Poison Control Center right away.

Directions

■ for preparation of the skin prior to surgery, clean the affected area, remove the pad, apply to the operative site prior to surgery

■ for use as a first aid antiseptic, clean the affected area, apply a small amount of this product on the area 1-3 times daily ■ may be covered with a sterile bandage ■ if bandaged, let dry first

Other Information

■ store at room temperature:15-30C (59-86F)

Inactive Ingredients

Citric Acid Monohydrate, Sodium Phosphate Dibasic, Water